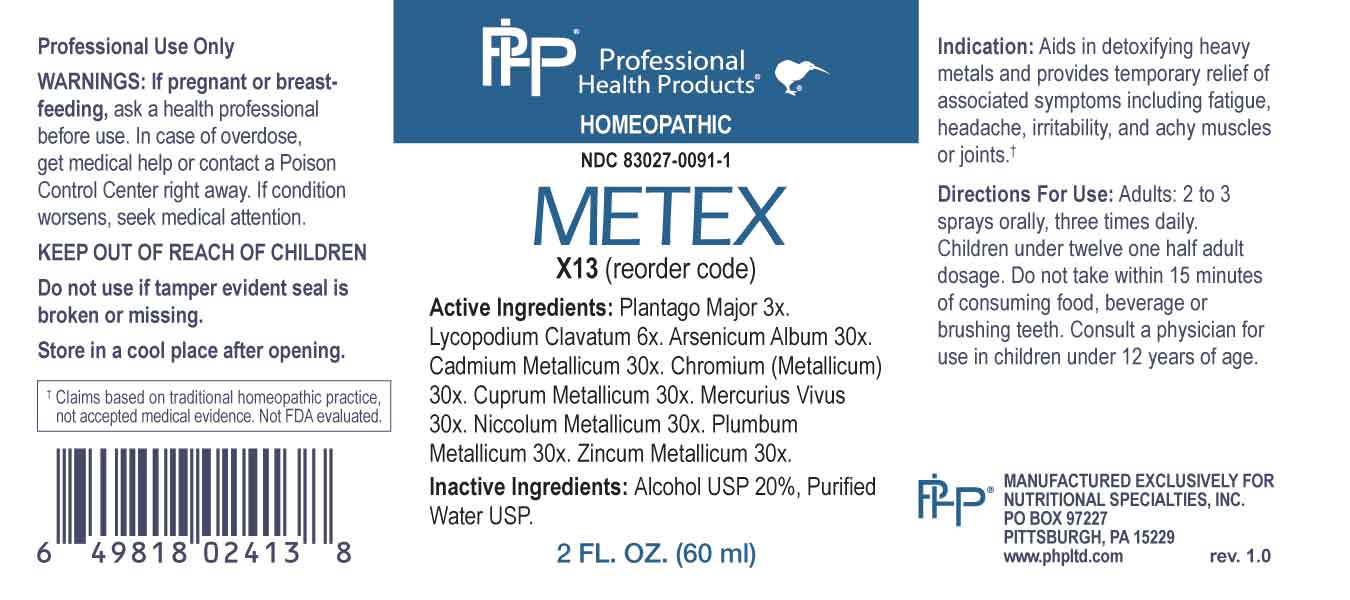 DRUG LABEL: Metex
NDC: 83027-0091 | Form: SPRAY
Manufacturer: Nutritional Specialties, Inc.
Category: homeopathic | Type: HUMAN OTC DRUG LABEL
Date: 20230711

ACTIVE INGREDIENTS: PLANTAGO MAJOR WHOLE 3 [hp_X]/1 mL; LYCOPODIUM CLAVATUM SPORE 6 [hp_X]/1 mL; ARSENIC TRIOXIDE 30 [hp_X]/1 mL; CADMIUM 30 [hp_X]/1 mL; CHROMIUM 30 [hp_X]/1 mL; COPPER 30 [hp_X]/1 mL; MERCURY 30 [hp_X]/1 mL; NICKEL 30 [hp_X]/1 mL; LEAD 30 [hp_X]/1 mL; ZINC 30 [hp_X]/1 mL
INACTIVE INGREDIENTS: WATER; ALCOHOL

DRUG FACTS:

ACTIVE INGREDIENTS:

Plantago Major 3X, Lycopodium Clavatum 6X, Arsenicum Album 30X, Cadmium Metallicum 30X, Chromium (Metallicum) 30X, Cuprum Metallicum 30X, Mercurius Vivus 30X, Niccolum Metallicum 30X, Plumbum Metallicum 30X, Zincum Metallicum 30X.

PURPOSE:

Aids in detoxifying heavy metals and provides temporary relief of associated symptoms including fatigue, headache, irritability, and achy muscles or joints.†

†Claims based on traditional homeopathic practice, not accepted medical evidence. Not FDA evaluated.

WARNINGS:

Professional Use Only

If pregnant or breast-feeding, ask a health professional before use.

In case of overdose, get medical help or contact a Poison Control Center right away.

If condition worsens, seek medical attention.

KEEP OUT OF REACH OF CHILDREN

Do not use if tamper evident seal is broken or missing.

Store in a cool place after opening

KEEP OUT OF REACH OF CHILDREN:

In case of overdose, get medical help or contact a Poison Control Center right away.

DIRECTIONS:

Adults: 2 to 3 sprays orally, three times daily. Children under twelve one half adult dosage. Do not take within 15 minutes of consuming food, beverage or brushing teeth. Consult a physician for use in children under 12 years of age.

INDICATIONS

Aids in detoxifying heavy metals and provides temporary relief of associated symptoms including fatigue, headache, irritability, and achy muscles or joints.†

†Claims based on traditional homeopathic practice, not accepted medical evidence. Not FDA evaluated.

INACTIVE INGREDIENTS:

Alcohol USP 20%, Purified Water USP.

QUESTIONS:

MANUFACTURED EXCLUSIVELY FOR

NUTRITIONAL SPECIALTIES, INC.

PO BOX 97227

PITTSBURG, PA 15229

www.phpltd.com

PACKAGE LABEL DISPLAY:

Professional

Health Products

HOMEOPATHIC

NDC 83027-0091-1

METEX

2 FL. OZ (60 ml)